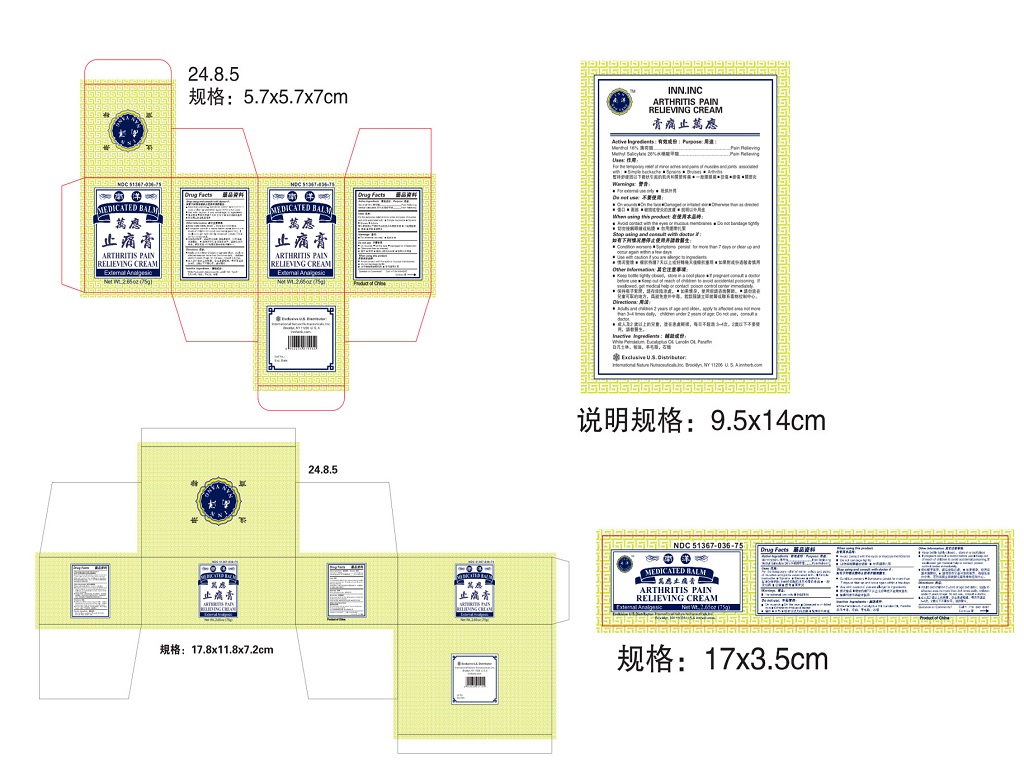 DRUG LABEL: Arthritis Pain Relieving Cream
NDC: 51367-036 | Form: CREAM
Manufacturer: International Nature Nutraceuticals, Inc.
Category: otc | Type: HUMAN OTC DRUG LABEL
Date: 20251227

ACTIVE INGREDIENTS: MENTHOL 12 g/1 1; METHYL SALICYLATE 19.5 g/1 1
INACTIVE INGREDIENTS: WHITE PETROLATUM; EUCALYPTUS OIL; LANOLIN OIL; PARAFFIN

Drug Facts

Active Ingredients

Menthol- 16%

Methyl Salicylate- 26%

Uses

For the temporary relief of minor aches and pains of muscles and joints associated with

- Simple backache
- Sprains
- Bruises
- Arthritis

Warnings

For external use only

Do not use

- On wounds
- On the face
- Damaged or irritated skin
- Otherwise than as directed

When using this product

- Avoid contact with the eyes, mouth or mucous membranes
- Do not bandage tightly

Stop using and consult with doctor if:

- Condition worsens
- Symptoms persist for more than 7 days or clear up and occur again within a few days.
- Use with caution if you are allergic to ingredients

Other Information

Keep bottle tightly closed, store in a cool place

If swallowed, get medical help or contact poison control center immediately

Directions

- Adults and children 2 years of age and older: apply to affected area not more than 3-4 times daily, children under 2 years of age: Do not use, consult a doctor

Inactive Ingredients

White Petrolatum, Eucalyptus Oil, Lanolin Oil, Paraffin